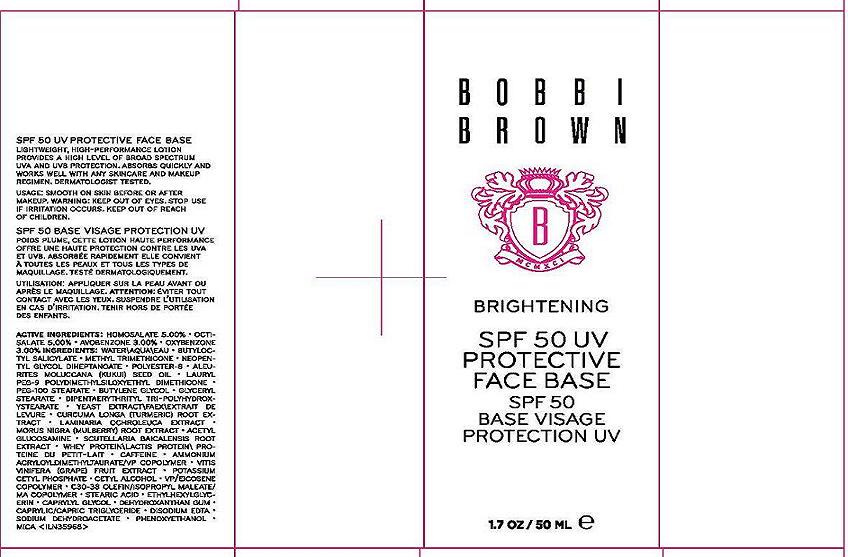 DRUG LABEL: BOBBI BROWN BRIGHTENING PROTECTIVE FACE BASE
NDC: 64141-005 | Form: CREAM
Manufacturer: Bobbi Brown Professional Cosmetics Inc.
Category: otc | Type: HUMAN OTC DRUG LABEL
Date: 20100713

ACTIVE INGREDIENTS: HOMOSALATE 5.0 mL/100 mL; OCTISALATE 5.0 mL/100 mL; AVOBENZONE 3.0 mL/100 mL; OXYBENZONE 3.0 mL/100 mL

ACTIVE INGREDIENT

ACTIVE INGREDIENTS: HOMOSALATE 5.00% [] OCTISALATE 5.00% [] AVOBENZONE 3.00% [] OXYBENZONE 3.00%

WHEN USING

DIRECTIONS: SMOOTH ON SKIN BEFORE OR AFTER MAKEUP

WARNINGS

KEEP OUT OF EYES. STOP USE IF IRRITATION OCCURS. KEEP OUT OF REACH OF CHILDREN.

PACKAGE LABEL

BOBBI BROWN

BRIGHTENING

SPF 50 UV

PROTECTIVE FACE BASE

1.7 OZ/50 ML

DIST. BOBBI BROWN PROFESSIONAL COSMETICS

NEW YORK, NY 10022